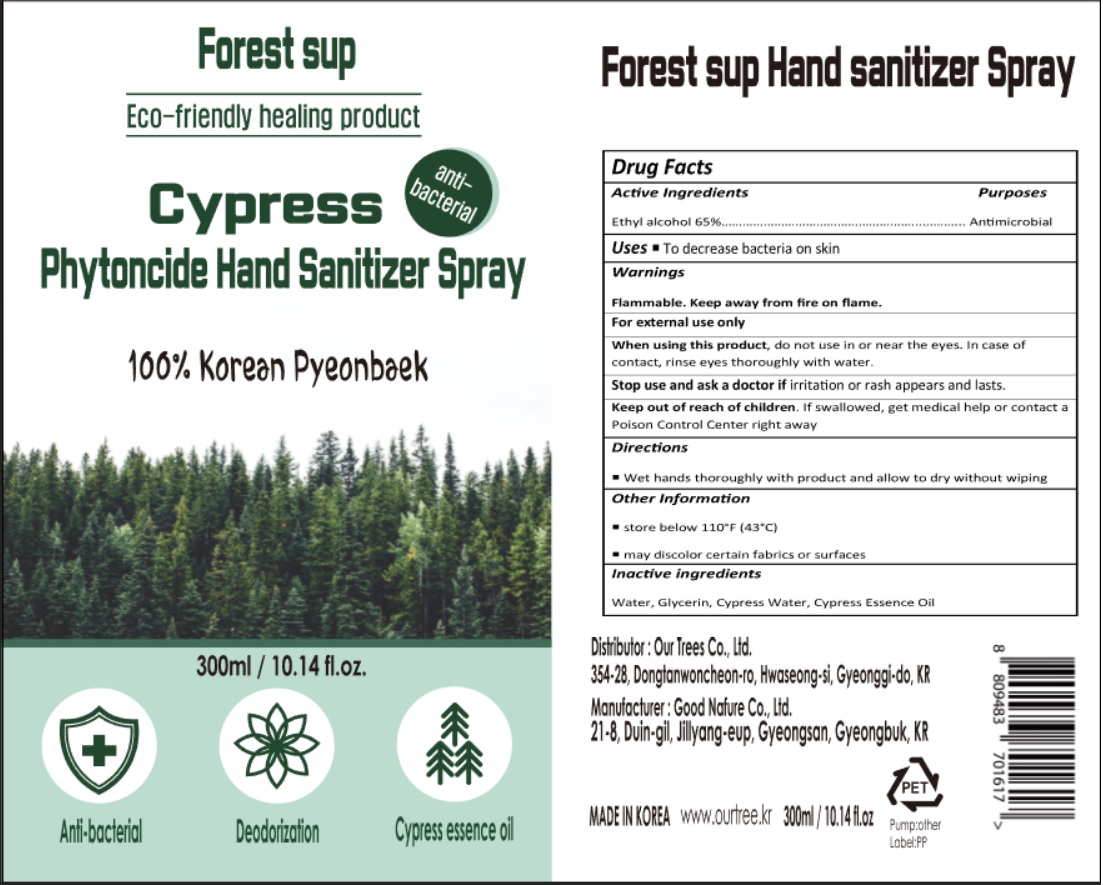 DRUG LABEL: Forest sup
NDC: 78799-001 | Form: SPRAY
Manufacturer: our tree co.ltd
Category: otc | Type: HUMAN OTC DRUG LABEL
Date: 20200625

ACTIVE INGREDIENTS: ALCOHOL 0.65 mL/1 mL
INACTIVE INGREDIENTS: WATER; GLYCERIN; CHAMAECYPARIS OBTUSA WOOD OIL; CUPRESSUS SEMPERVIRENS LEAF OIL

78799-001_Forest sup

Active ingredient

Ethyl alcohol 65%

Purpose

Antimicrobial

Use

- To decrease bacteria on skin

Warnings

Flammable. Keep away from fire or flame.

For external use only

When using this product do not use in or near the eyes. In case of contact, rinse eyes thoroughly with water.

Stop use and ask a doctor if irritation or rash appears and lasts

Keep out of reach of children.

Other information

- Store below 110°F (43°C)
- May discolor certain fabrics or surfaces

Directions

Wet hands thoroughly with product and allow to dry without wiping

Inactive ingredients

Water, Glycerin, Cypress Water, Cypress Essence Oil